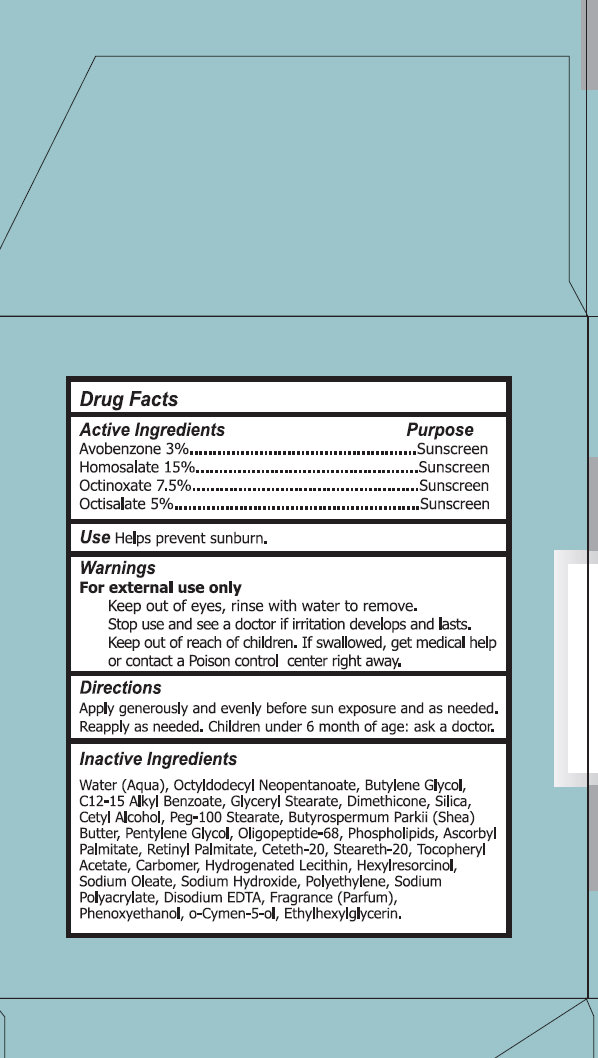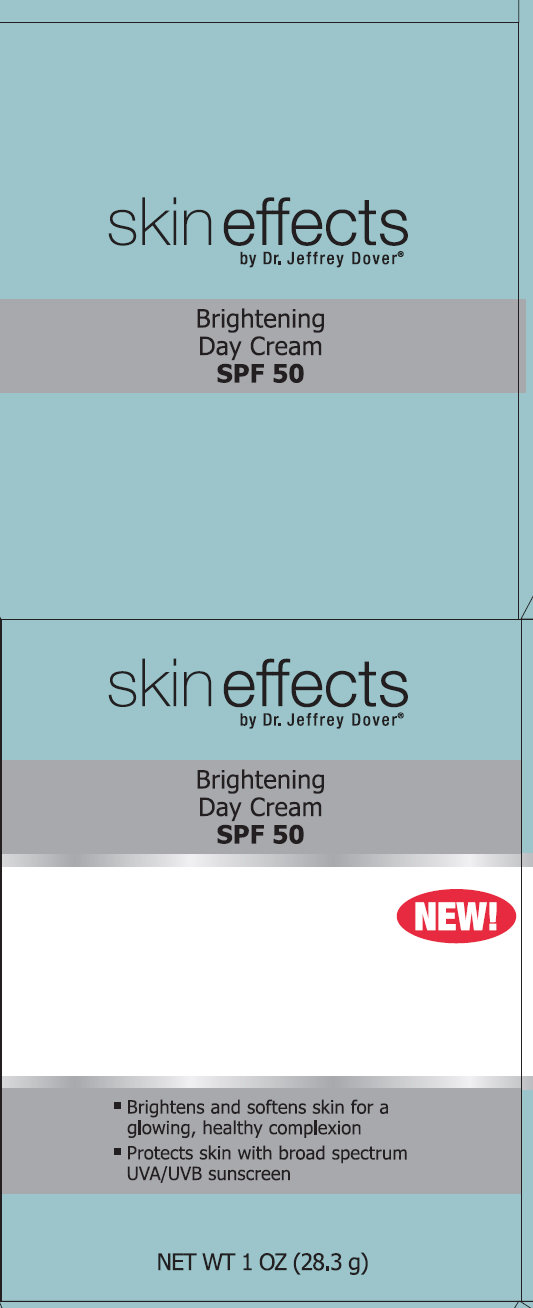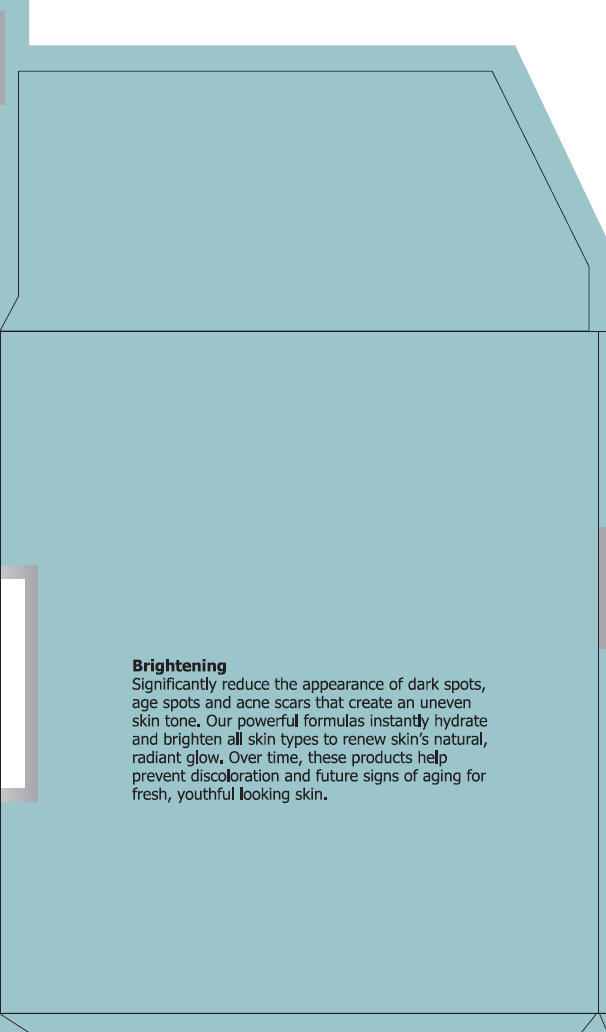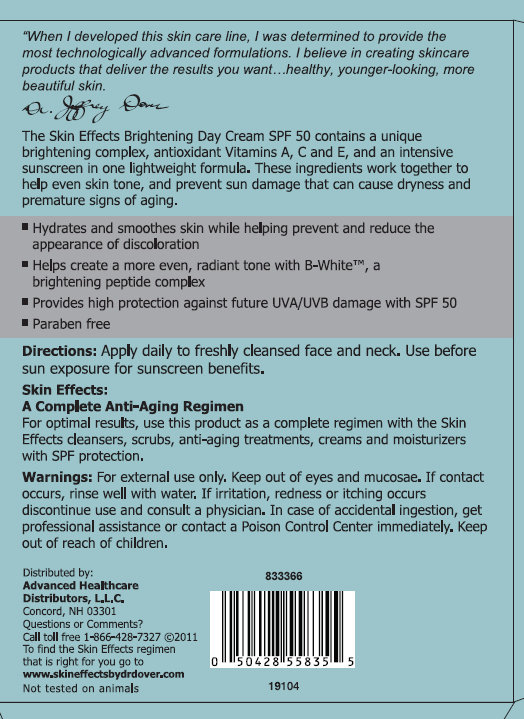 DRUG LABEL: skin effects Brightening Day SPF 50
NDC: 42877-002 | Form: CREAM
Manufacturer: Diversified Global Technologies DBA Diversified Distribution
Category: otc | Type: HUMAN OTC DRUG LABEL
Date: 20111012

ACTIVE INGREDIENTS: AVOBENZONE 3 g/100 g; HOMOSALATE 15 g/100 g; OCTINOXATE 7.5 g/100 g; OCTISALATE 5 g/100 g
INACTIVE INGREDIENTS: WATER; OCTYLDODECYL NEOPENTANOATE; BUTYLENE GLYCOL; ALKYL (C12-15) BENZOATE; GLYCERYL MONOSTEARATE; DIMETHICONE; SILICON DIOXIDE; CETYL ALCOHOL; PEG-100 STEARATE; SHEA BUTTER; PENTYLENE GLYCOL; EGG PHOSPHOLIPIDS; ASCORBYL PALMITATE; VITAMIN A PALMITATE; CETETH-20; STEARETH-20; .ALPHA.-TOCOPHEROL ACETATE, D- ; HEXYLRESORCINOL; SODIUM OLEATE; SODIUM HYDROXIDE; HIGH DENSITY POLYETHYLENE; EDETATE DISODIUM; PHENOXYETHANOL; O-CYMEN-5-OL; ETHYLHEXYLGLYCERIN

skin effects Brightening Day Cream SPF 50

Active Ingredients

Avobenzone 3%

Homosalate 15%

Octinoxate 7.5%

Octisalate 5%

Purpose

Sunscreen

Use

Helps prevent sunburn

Warnings

For external use only

Keep out of eyes, rinse with water to remove.

Stop use and see a doctor if irritation develops and lasts.

Keep out of reach of children. If swallowed, get medical help or contact a Poison Control center right away.

Directions

Apply generously and evenly before sun exposure and as needed.

Reapply as needed.

Children under 6 months of age: Ask a doctor.

Inactive Ingredients

Water (Aqua), Octyldodecyl Neopentanoate, Butylene Glycol, C12-15 Alkyl Benzoate, Glyceryl Stearate, Dimethicone, Silica, Cetyl Alcohol, PEG-100 Stearate, Butyrospermum Parkii (Shea) Butter, Pentylene Glycol, Oligopeptide-68, Phospholipids, Ascorbyl Palmitate, Retinyl Palmitate, Ceteth-20, Steareth-20, Tocopheryl Acetate, Carbomer, Hydrogenated Lecithin, Hexylresorcinol, Sodium Oleate, Sodium Hydroxide, Polyethylene, Sodium Polyacrylate, Disodium EDTA, Fragrance (Parfum), Phenoxyethanol, o-Cymen05-ol, Ethylhexylgylcerin.

Brightening

Significantly reduce the appearance of dark spots, age spots and acne scars that create an uneven skin tone. Our powerful formulas instantly hydrate and brighten all skin types to renew skin's natural radiant glow. Over time, these products help prevent discoloration and future signs of aging for fresh, youthful looking skin.

Skin Effects Brightening Day Cream SPF 50 1oz / 28.3g

"When I developed this skin care line, I was determined to provide the most technologically advanced formulations. I believe in creating skin care products that deliver the results you want, healthy, younger-looking, more beautiful skin." Dr. Jeffrey Dover
The Skin Effects Firming Facial Cream with Retinol Complex SPF 30 contains retinol, advanced hydration and SPF protection. This trio of powerful ingredients is time-released to improve brightness, firmness, moisture and skin tone. Antioxidant Vitamins C and E condition skin and help protect against free radicals.

- Unique formula causes less irritation than most retinol-based products
- Helps moisturize, firm and renew skin's surface for a smoother tone and texture
- Provides high protection against future UVA/UVB damage with SPF 30
- Paraben free

Directions:

Apply daily to freshly cleansed face and neck. Use before sun exposure for sunscreen benefits.

Skin Effects: A Complete Anti-Aging Regimen

For optimal results, use this product as a complete regimen with the Skin Effects cleansers, scrubs, anti-aging treatments, creams and moisturizes with SPF protection.

Warnings:

For external use only. Keep out of eyes and mucosa. If contact occurs, rinse well with water. If irritation, redness or itching occurs discontinue use and consult a physician. In case of accidental ingestion, get professional assistance or contact a Poison Control Center immediately. Keep out of reach of children. For external use only. Keep out of eyes, rinse with water to remove. Stop use and see a doctor if irritation develops and lasts. Keep out of reach of children.

Distributed by:

Advanced Healthcare Distributors, L.L.C.

Concord, NH 03301

Questions or Comments?

Call Toll Free 1-866-428-7327

To find the Skin Effects regimen that is right for you go to

www.skineffectsbydrdover.com

Not tested on animals

skin effects Brightening Day Cream SPF 50 1oz / 28.3g

skin effects

by Dr. Jeffrey Dover

Brightening Day Cream SPF 50

- Brightens and softens skin for a glowing, healthy complexion
- Protects skin with broad spectrum UVA/UVB sunscreen

NET WT 1 OZ (28.3g)